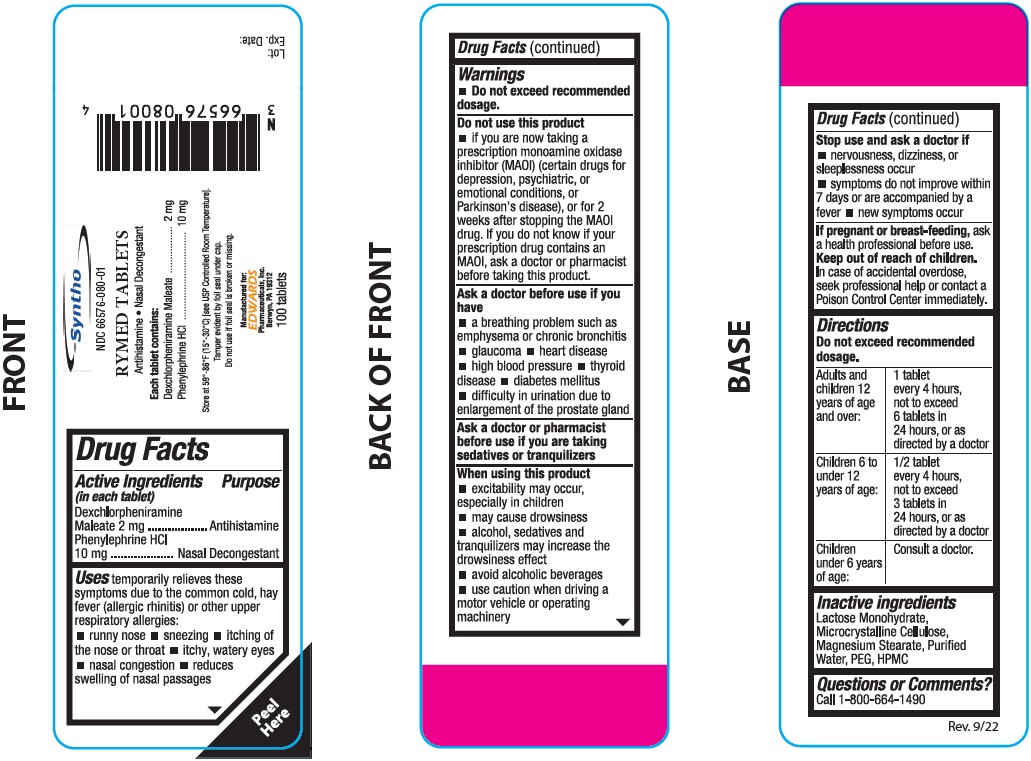 DRUG LABEL: Dexchlorpheniramine Maleate, Phenylephrine HCl
NDC: 66576-080 | Form: TABLET
Manufacturer: Syntho Pharmaceuticals Inc.
Category: otc | Type: HUMAN OTC DRUG LABEL
Date: 20221103

ACTIVE INGREDIENTS: PHENYLEPHRINE HYDROCHLORIDE 10 mg/1 1; DEXCHLORPHENIRAMINE MALEATE 2 mg/1 1
INACTIVE INGREDIENTS: LACTOSE MONOHYDRATE; MICROCRYSTALLINE CELLULOSE; MAGNESIUM STEARATE; WATER; POLYETHYLENE GLYCOL; HYPROMELLOSE, UNSPECIFIED

RYMED TABLETS

Active Ingredients (in each tablet)

1. Dexchlorpheniramine Maleate - 2 mg
2. Phenylephrine HCl - 10 mg

Inactive ingredients

Lactose Monohydrate, Microcrystalline Cellulose, Magnesium Stearate, Purified Water, PEG, HPMC

Purpose

1. Dexchlorpheniramine Maleate 2 mg - Antihistamine
2. Phenylephrine HCl 10 mg - Nasal Decongestant

Uses

temporarily relieves these symptoms due to the common cold, hay fever (allergic rhinitis) or other upper respiratory allergies:
■ runny nose
■ sneezing
■ itching of the nose or throat
■ itchy, watery eyes
■ nasal congestion
■ reduces swelling of nasal passages

Warnings

■ Do not exceed recommended dosage.
Do not use this product
■ if you are now taking a prescription monoamine oxidase inhibitor (MAOI) (certain drugs for depression, psychiatric, or emotional conditions, or Parkinson's disease), or for 2 weeks after stopping the MAOI drug. If you do not know if your prescription drug contains an MAOI, ask a doctor or pharmacist before taking this product.
Ask a doctor before use if you have
■ a breathing problem such as emphysema or chronic bronchitis
■ glaucoma
■ heart disease
■ high blood pressure
■ thyroid disease
■ diabetes mellilus
■ difficulty in urination due to enlargement of the prostate gland
Ask a doctor or pharmacist before use if you are taking sedatives or tranquilizers
When using this product
■ excitability may occur, especially in children
■ may cause drowsiness
■ alcohol, sedatives and tranquilizers may increase the drowsiness effect
■ avoid alcoholic beverages
■ use caution when driving a motor vehicle or operating machinery
Stop use and ask a doctor if
■ nervousness, dizziness, or sleeplessness occur
■ symptoms do not improve within 7 days or are accompanied by a fever
■ new symptoms occur
If pregnant or breast-feeding, ask a health professional before use.
Keep out of reach of children.In case of accidental overdose, seek professional help or contact a Poison Control Center immediately.

Directions

Do not exceed recommended dosage.

Adults and children 12 years of age and over: | 1 tablet every 4 hours, not to exceed 6 tablets in 24 hours, or as directed by a doctor
Children 6 to under 12 years of age: | 1/2 tablet every 4 hours, not to exceed 3 tablets in 24 hours, or as directed by a doctor
Children under 6 years of age: | Consult a doctor.

Questions or Comments?

Call 1-800-664-1490

PACKAGE LABEL.PRINCIPAL DISPLAY PANEL

Rymed Tablets - NDC 66576-080-01 - 100's Bottle Label